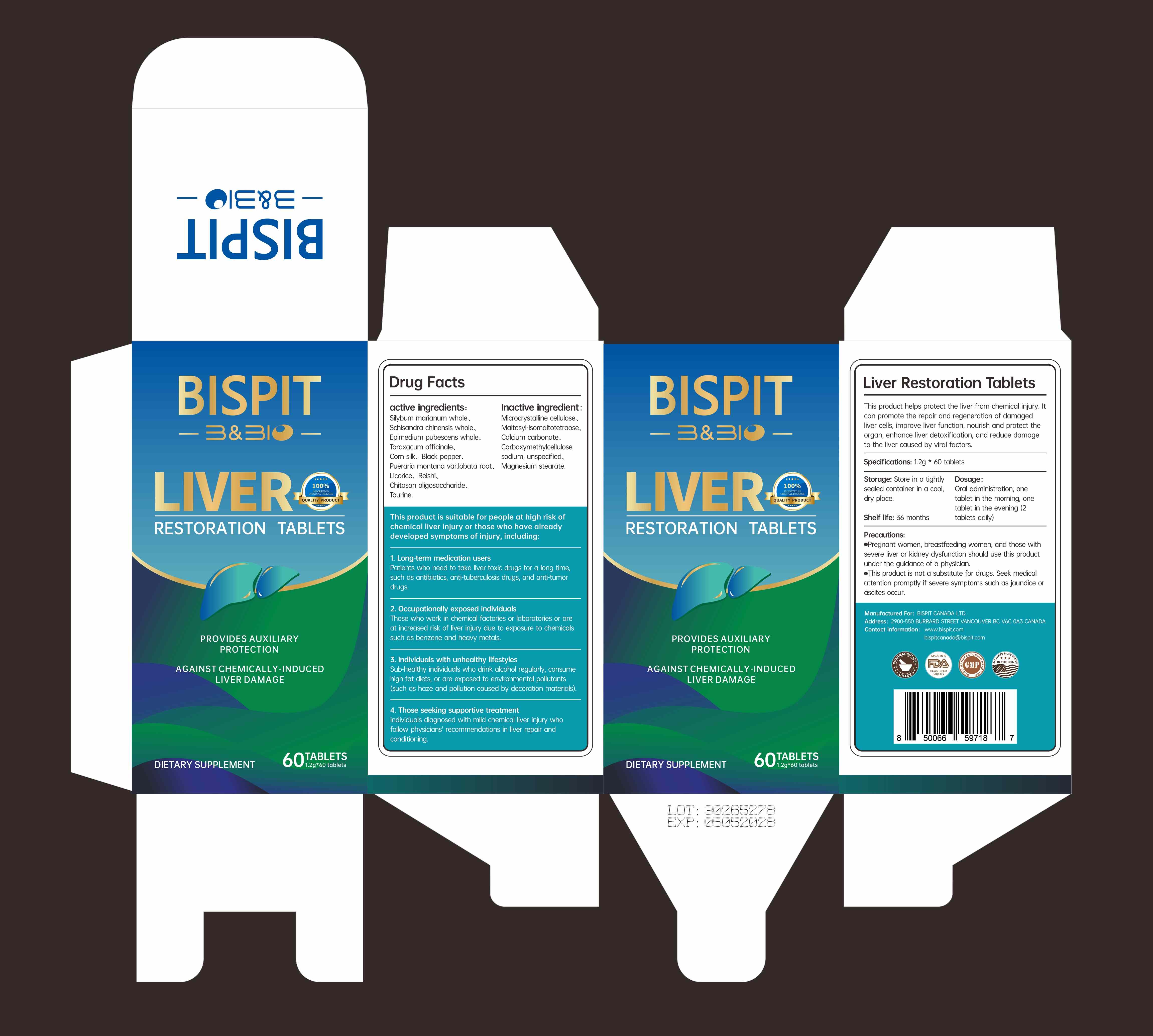 DRUG LABEL: Bispit Canada Ltd.
NDC: 85631-002 | Form: TABLET
Manufacturer: Bispit Canada Ltd.
Category: homeopathic | Type: HUMAN OTC DRUG LABEL
Date: 20250606

ACTIVE INGREDIENTS: EPIMEDIUM PUBESCENS WHOLE 120 mg/1.2 g; BLACK PEPPER 60 mg/1.2 g; TARAXACUM MONGOLICUM 180 mg/1.2 g; PUERARIA MONTANA VAR. LOBATA ROOT 60 mg/1.2 g; CHITOSAN OLIGOSACCHARIDE 12 mg/1.2 g; SCHISANDRA CHINENSIS WHOLE 240 mg/1.2 g; SILYBUM MARIANUM WHOLE 300 mg/1.2 g; GANODERMA LUCIDUM WHOLE 48 mg/1.2 g; TAURINE 12 mg/1.2 g; LICORICE 24 mg/1.2 g
INACTIVE INGREDIENTS: CARBOXYMETHYLCELLULOSE SODIUM, UNSPECIFIED; MAGNESIUM STEARATE; CALCIUM CARBONATE; MICROCRYSTALLINE CELLULOSE; MALTOSYL-ISOMALTOTETRAOSE

ACTIVE INGREDIENT

SILYBUM MARIANUM WHOLE
SCHISANDRA CHINENSIS WHOLE
EPIMEDIUM PUBESCENS WHOLE
TARAXACUM MONGOLICUM WHOLE
BLACK PEPPER
PUERARIA MONTANA VAR. LOBATA ROOT
LICORICE
GANODERMA LUCIDUM WHOLE
CHITOSAN OLIGOSACCHARIDE
TAURINE

PURPOSE

This product helps protect the liver from chemical injury. ltcan promote the repair and regeneration of damagedliver cells, improve liver function, nourish and protect theorgan, enhance liver detoxification, and reduce damageto the liver caused by viral factors.

KEEP OUT OF REACH OF CHILDREN

DOSAGE & ADMINISTRATION

Dosage:Oral administration, onetablet in the morning, onetablet in the evening (2tablets daily)

INDICATIONS & USAGE

This product is suitable for people at high risk ofchemical liver injury or those who have alreadydeveloped symptoms of injury, including:
1. Long-term medication usersPatients who need to take liver-toxic drugs for a long timesuch as antibiotics, anti-tuberculosis drugs, and anti-tumordrugs.
2.Occupationally exposed individualsThose who work in chemical factories or laboratories or areat increased risk of liver injury due to exposure to chemicalssuch as benzene and heavy metals.
3. individuals with unhealthy lifestylesSub-healthy individuals who drink alcohol regularly, consumehigh-fat diets, or are exposed to environmental pollutants(such as haze and pollution caused by decoration materials).
4. Those seeking supportive treatmentIndividuals diagnosed with mild chemical liver injury whofollow physicians" recommendations in liver repair andconditioning.

WARNINGS

Pregnant women, breastfeeding women, and those withsevere liver or kidney dysfunction should use this productunder the guidance of a physician.

This product is not a substitute for drugs. Seek medicalattention promptly if severe symptoms such as jaundice orascites occur.

OTHER SAFETY INFORMATION

Storage: Store in a tightlysealed container in a cool,dry place.

INACTIVE INGREDIENT

MICROCRYSTALLINE CELLULOSE
MALTOSYL-ISOMALTOTETRAOSE
CALCIUM CARBONATE
CARBOXYMETHYLCELLULOSE SODIUM, UNSPECIFIED
MAGNESIUM STEARATE